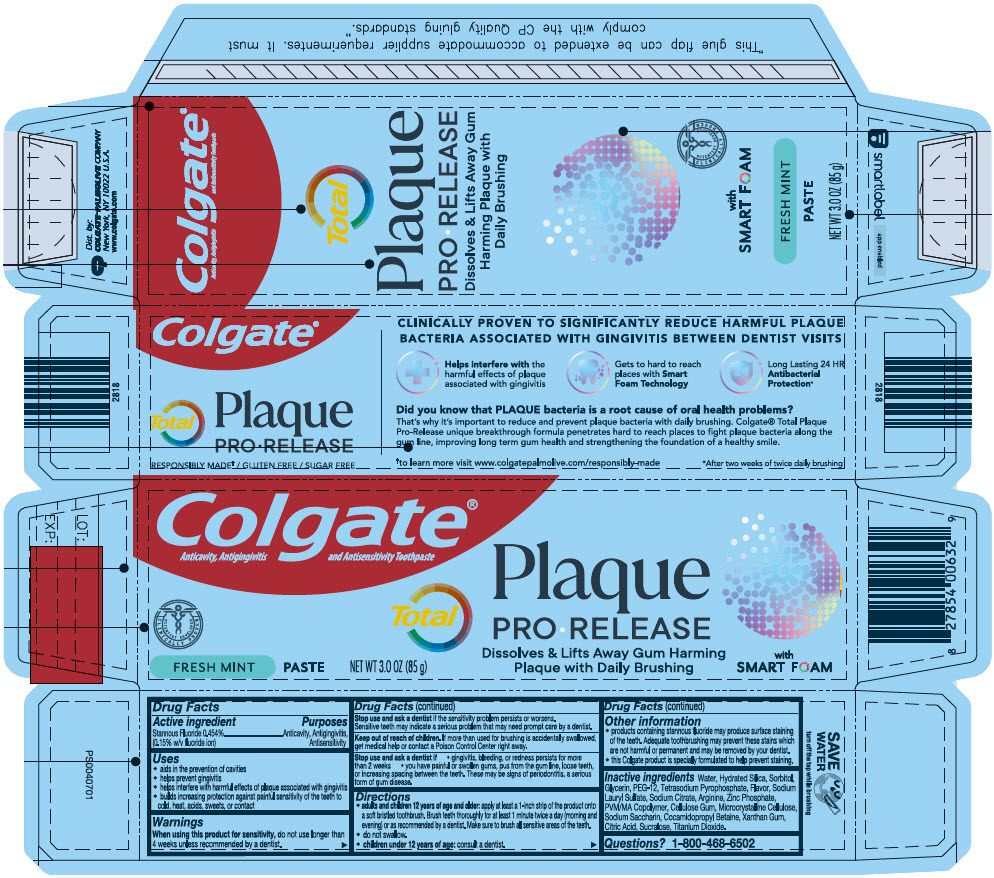 DRUG LABEL: Colgate Total Plaque Pro Release Fresh Mint
NDC: 35000-180 | Form: PASTE, DENTIFRICE
Manufacturer: Colgate-Palmolive Company
Category: otc | Type: HUMAN OTC DRUG LABEL
Date: 20250912

ACTIVE INGREDIENTS: STANNOUS FLUORIDE 1.1 mg/1 g
INACTIVE INGREDIENTS: WATER; SORBITOL; HYDRATED SILICA; GLYCERIN; POLYETHYLENE GLYCOL 600; SODIUM PYROPHOSPHATE; SODIUM LAURYL SULFATE; SODIUM CITRATE, UNSPECIFIED FORM; ARGININE; ZINC PHOSPHATE; METHYL VINYL ETHER AND MALEIC ACID COPOLYMER (1750000 WAMW); CARBOXYMETHYLCELLULOSE SODIUM, UNSPECIFIED; MICROCRYSTALLINE CELLULOSE; SACCHARIN SODIUM; COCAMIDOPROPYL BETAINE; XANTHAN GUM; ANHYDROUS CITRIC ACID; SUCRALOSE; TITANIUM DIOXIDE

Colgate® Total Plaque Pro Release Fresh Mint

Drug Facts

Active ingredient

Stannous Fluoride 0.454% (0.15% w/v fluoride ion)

Purposes

Anticavity, Antigingivitis, Antisensitivity

Uses

- aids in the prevention of cavities
- helps prevent gingivitis
- helps interfere with harmful effects of plaque associated with gingivitis
- builds increasing protection against painful sensitivity of the teeth to cold, heat, acids, sweets, or contact

Warnings

When using this product for sensitivity, do not use longer than 4 weeks unless recommended by a dentist.

Stop use and ask a dentist if the sensitivity problem persists or worsens. Sensitive teeth may indicate a serious problem that may need prompt care by a dentist.

Keep out of reach of children. If more than used for brushing is accidentally swallowed, get medical help or contact a Poison Control Center right away.

Stop use and ask a dentist if

- gingivitis, bleeding, or redness persists for more than 2 weeks
- you have painful or swollen gums, pus from the gum line, loose teeth, or increasing spacing between the teeth. These may be signs of periodontitis, a serious form of gum disease.

Directions

- adults and children 12 years of age and older: apply at least a 1-inch strip of the product onto a soft bristled toothbrush. Brush teeth thoroughly for at least 1 minute twice a day (morning and evening) or as recommended by a dentist. Make sure to brush all sensitive areas of the teeth.
- do not swallow.
- children under 12 years of age: consult a dentist.

Other information

- products containing stannous fluoride may produce surface staining of the teeth. Adequate toothbrushing may prevent these stains which are not harmful or permanent and may be removed by your dentist.
- this Colgate product is specially formulated to help prevent staining.

Inactive ingredients

Water, Hydrated Silica, Sorbitol, Glycerin, PEG-12, Tetrasodium Pyrophosphate, Flavor, Sodium Lauryl Sulfate, Sodium Citrate, Arginine, Zinc Phosphate, PVM/MA Copolymer, Cellulose Gum, Microcrystalline Cellulose, Sodium Saccharin, Cocamidopropyl Betaine, Xanthan Gum, Citric Acid, Sucralose, Titanium Dioxide.

Questions?

1-800-468-6502

Dist. by:
COLGATE-PALMOLIVE COMPANY
New York, NY 10022 U.S.A.

PRINCIPAL DISPLAY PANEL - 85 g Tube Carton

Colgate®
Anticavity, Antigingivitis and Antisensitivity Toothpaste

SCIENTIST DEVELOPED
CLINICALLY PROVEN

FRESH MINT

PASTE

NET WT 3.0 OZ (85 g)

Total

Plaque

PRO • RELEASE

Dissolves & Lifts Away Gum Harming
Plaque with Daily Brushing

with
SMART FOAM